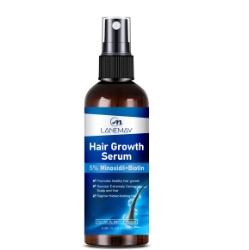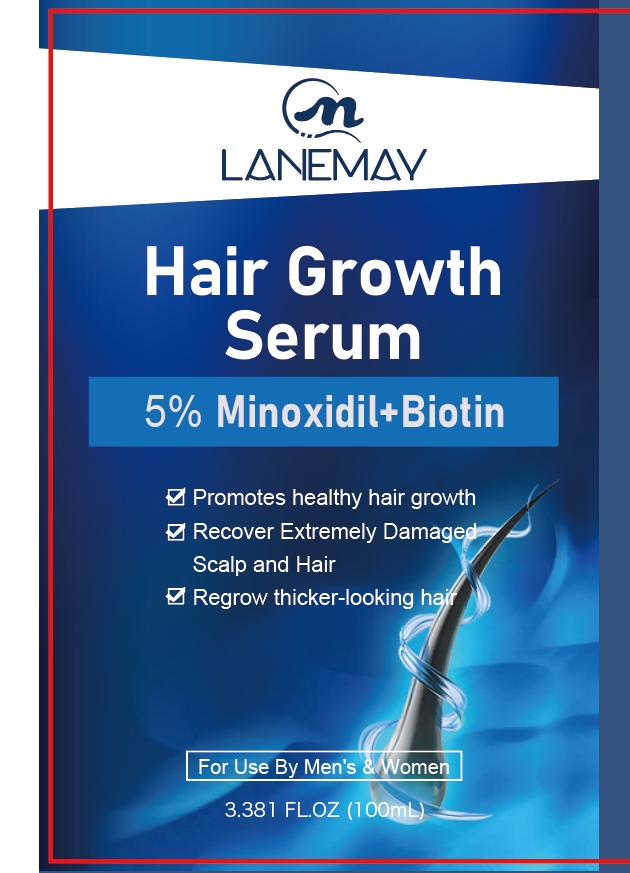 DRUG LABEL: Hair Growth Serum
NDC: 84025-063 | Form: LIQUID
Manufacturer: Guangzhou Yanxi Biotechnology Co., Ltd
Category: otc | Type: HUMAN OTC DRUG LABEL
Date: 20240711

ACTIVE INGREDIENTS: PROPANEDIOL 4 g/100 mL; MINOXIDIL 3 g/100 mL
INACTIVE INGREDIENTS: WATER

DOSAGE AND ADMINISTRATION

Use as a common essential oil

WARNINGS

Keep out of Children

INACTIVE INGREDIENT

Aqua

INDICATIONS AND USAGE

Use as a common essential oil

Keep out of Children

PURPOSE

You can change your hair more.